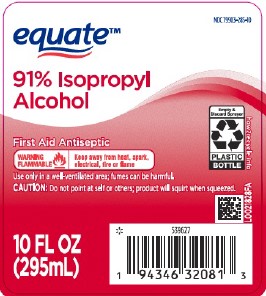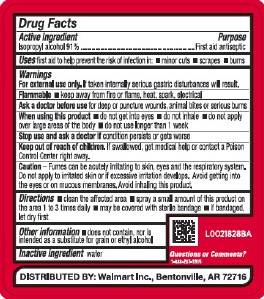 DRUG LABEL: Isopropyl Alcohol
NDC: 79903-285 | Form: LIQUID
Manufacturer: Walmart Inc.
Category: otc | Type: HUMAN OTC DRUG LABEL
Date: 20260227

ACTIVE INGREDIENTS: ISOPROPYL ALCOHOL 91 mL/100 mL
INACTIVE INGREDIENTS: WATER

Equate 804.003/804AA
91% Isopropyl Alcohol

Active ingredient

Isopropyl alcohol 91%

Purpose

First aid antiseptic

Uses

first aid to help prevent the risk of infection in:

- minor cuts
- scrapes
- burns

Warnings

For external use only.If taken internally serious gastric disturbances will result.

Flammable - keep away from fire or flame, heat, spark, electrical

Ask a doctor before use

for deep or puncture wounds, animal bites or serious burns

When using this product

- do not get into eyes
- do not inhale
- do not apply over large areas of the body
- do not use longer than 1 week

Stop use and ask a doctor if

condition persists or gets worse

Keep out of reach of children.

If swallowed, get medical help or contact a Poison Control Center right away.

Caution

Fumes can be acutely irritating to skin, eyes and the respiratory system. Do not apply to irritated skin or if excessive irritation develops. Avoid getting into the eyes or on mucous membranes. Avoid inhaling this product.

Directions

- clean the affected area
- spray a small amount of this product on the area 1 to 3 times daily
- may be covered with a sterile bandage
- if bandaged, let dry first

Other information

- does not contain, nor is intended as a substitute for grain or ethyl alcohol

Inactive ingredient

water

Questions or comments?

1-888-287-1915

Adverse Reaction

DISTRIBUTED BY: Walmart Inc., Bentonville, AR 72716

PACKAGE LABEL

NDC 79903-285-10

equate ™

91% Isopropyl Alcohol

First Aid Antiseptic

WARNING FLAMMABLE - Keep away from heat, spark, electrical, fire or flame

Use only in a well-ventilated area; fumes can be harmful.

CAUTION: Do not point at self or others; product will squirt when squeezed.

Empty & Discard Sprayer

PLASTIC BOTTLE

how2recycle.info

10 FL OZ (295 mL)